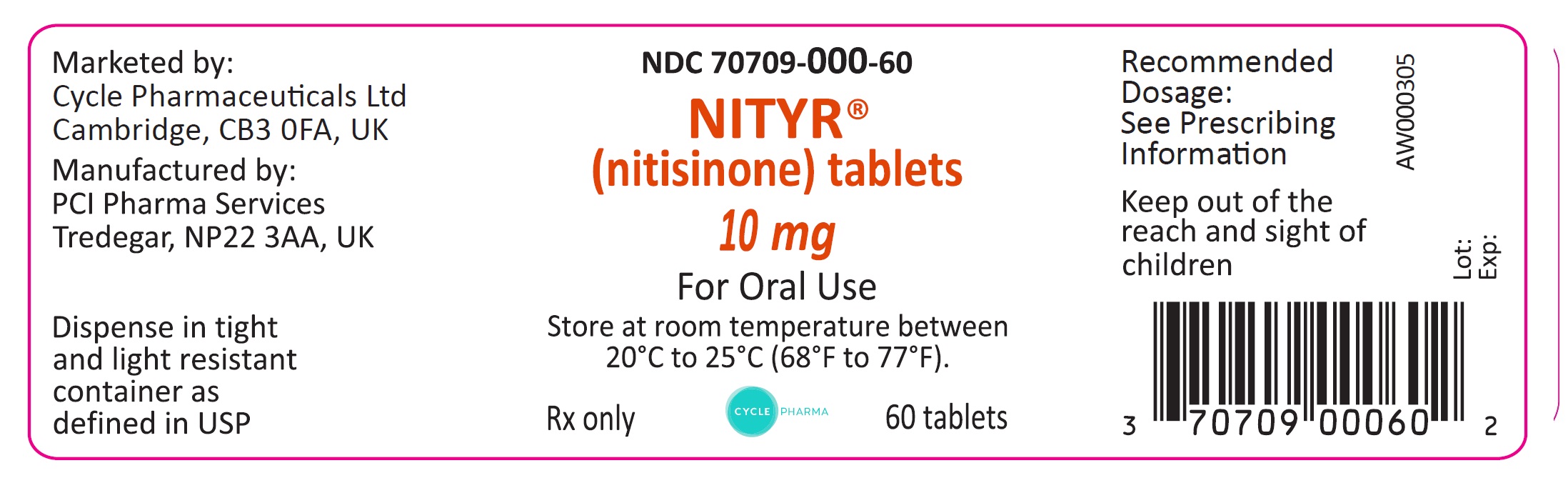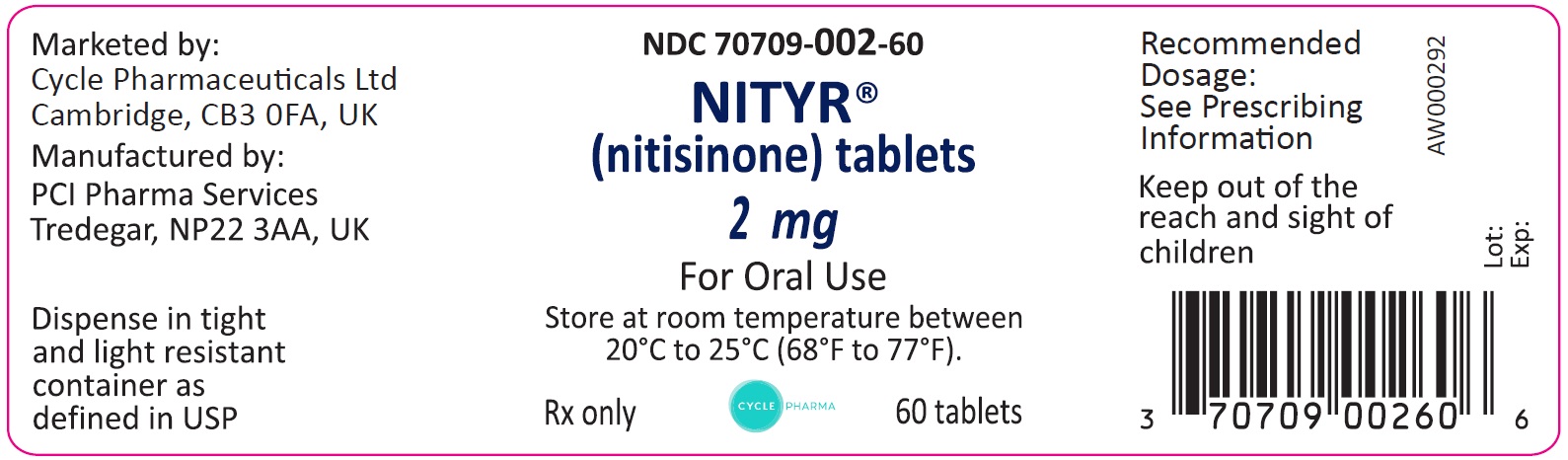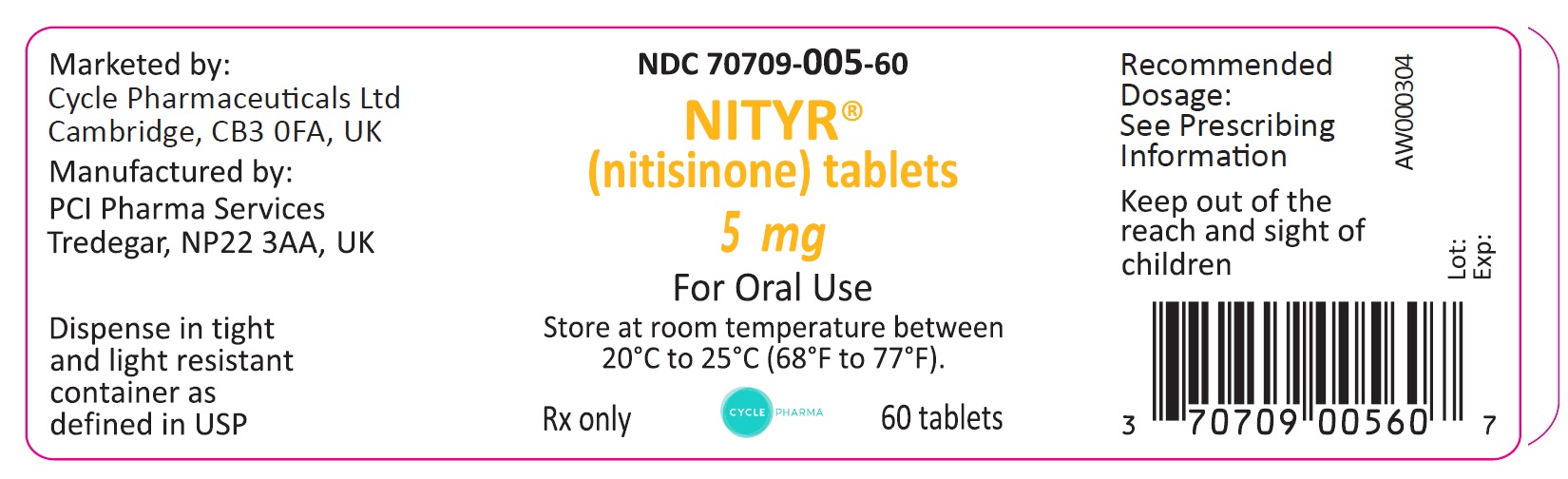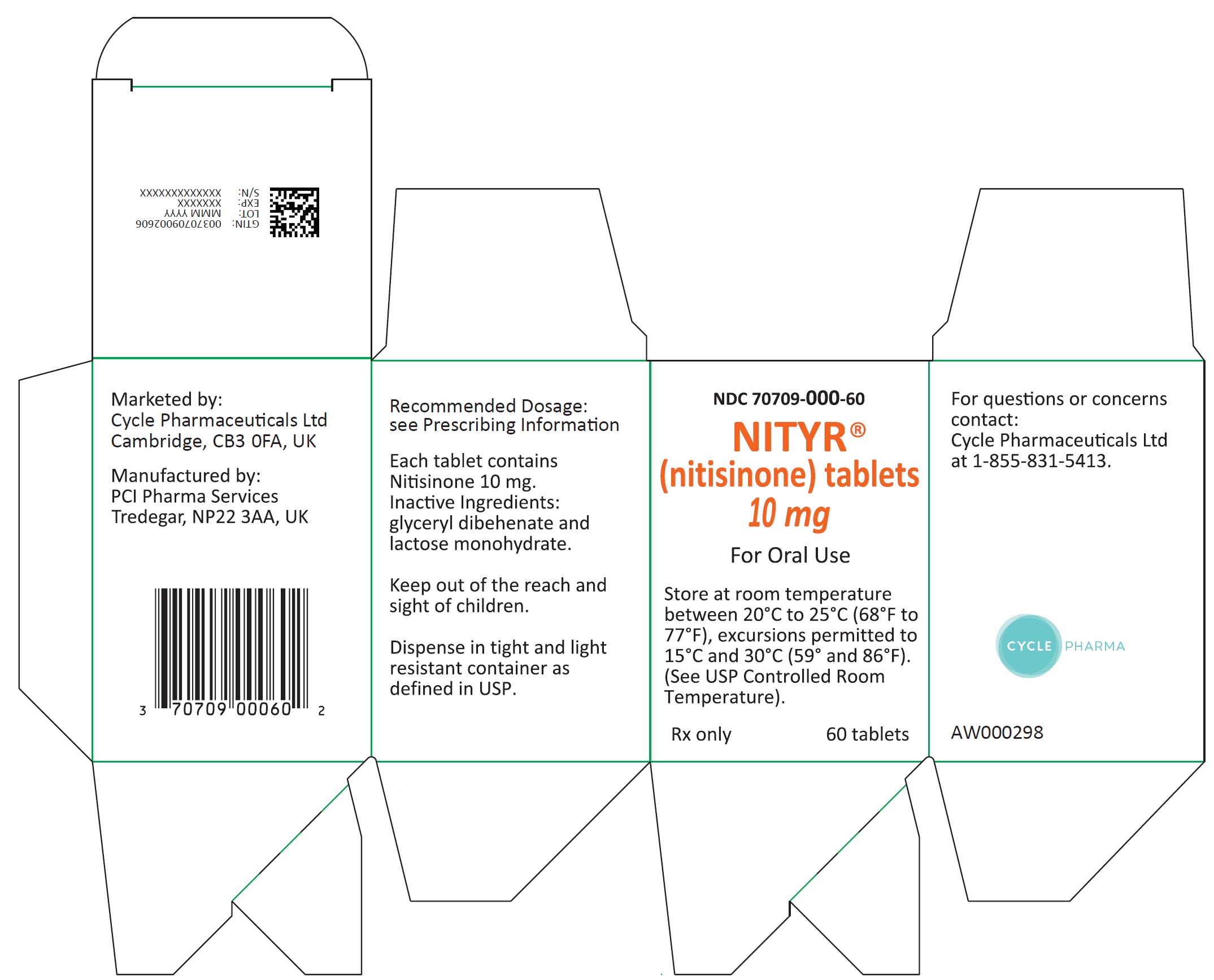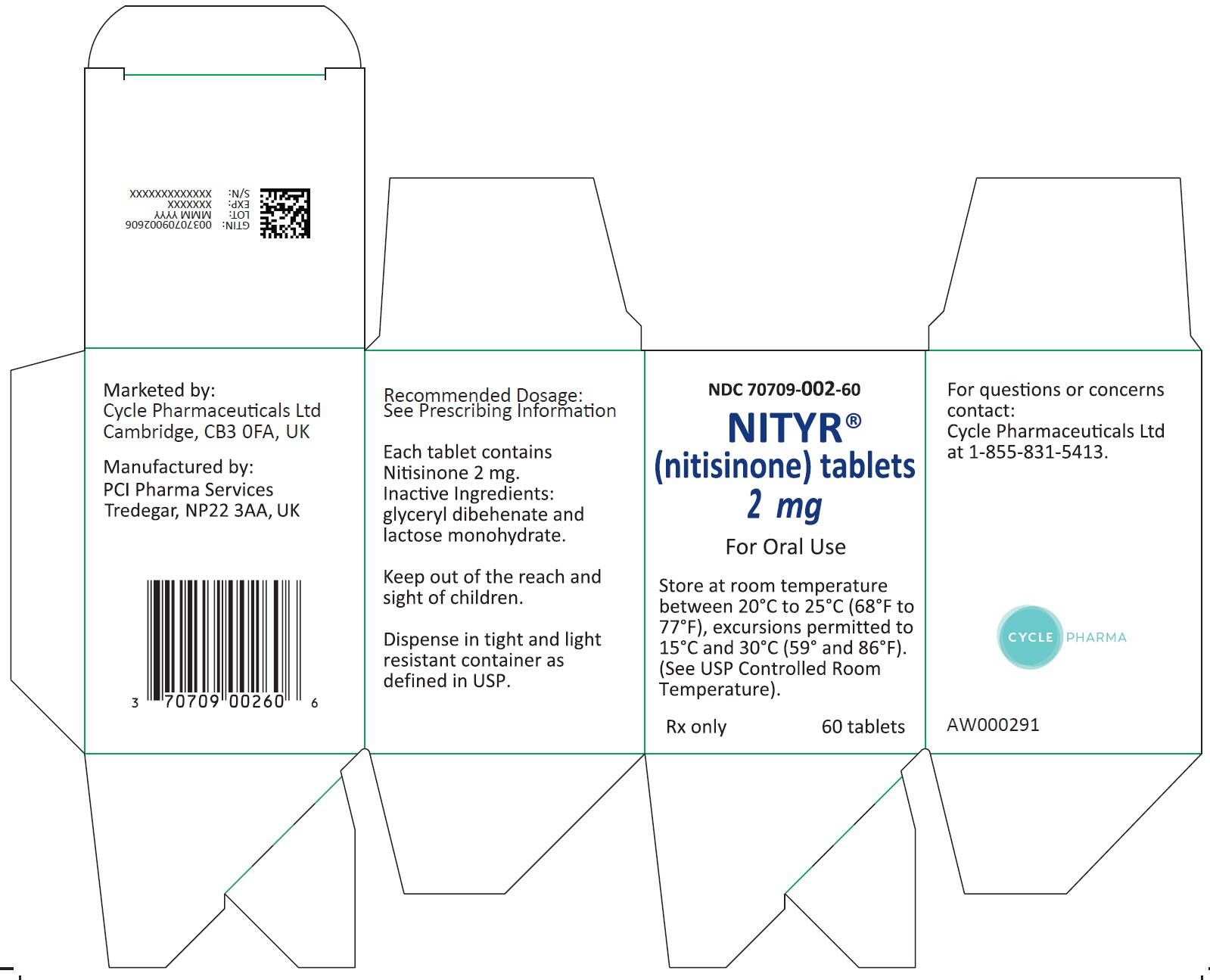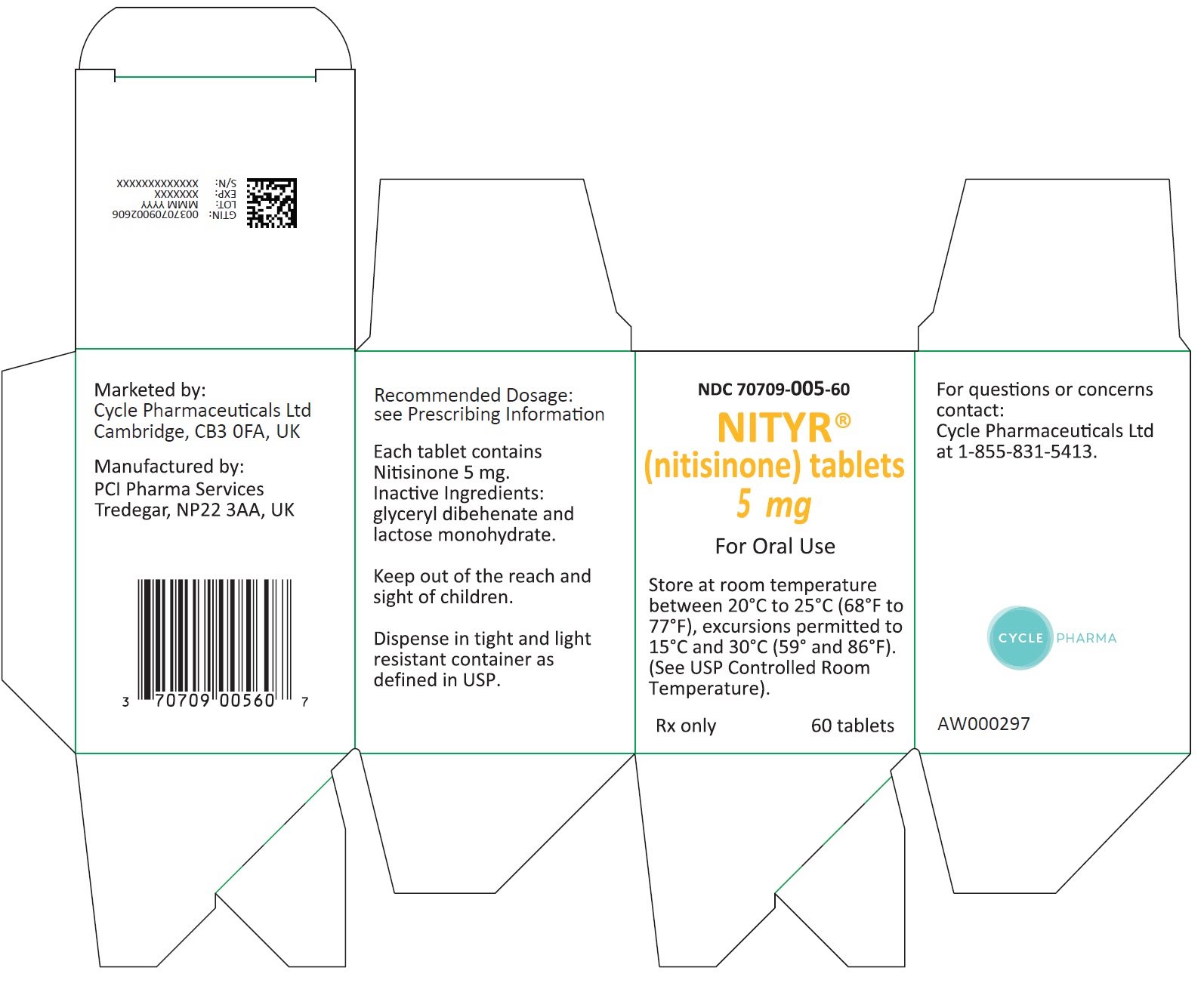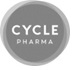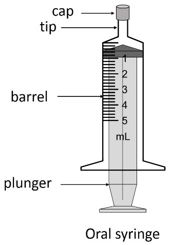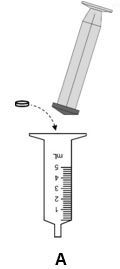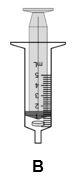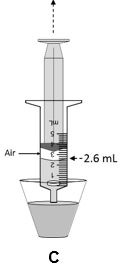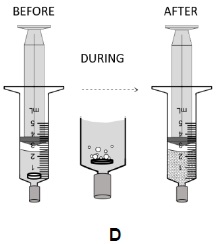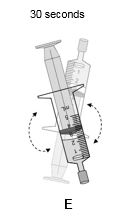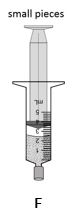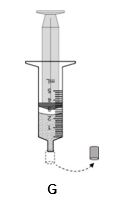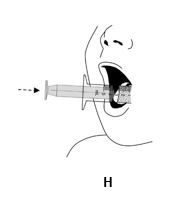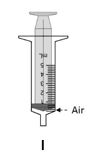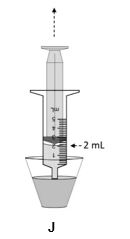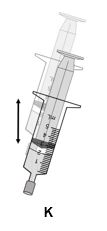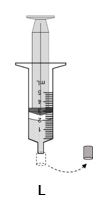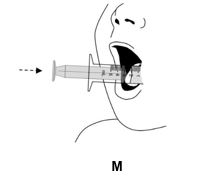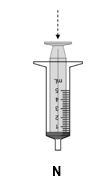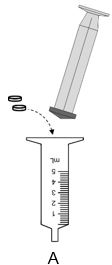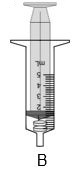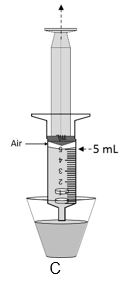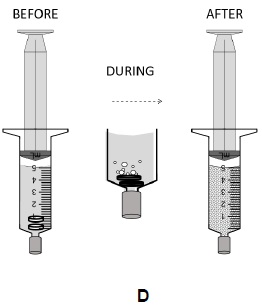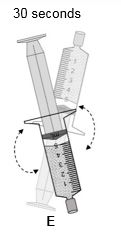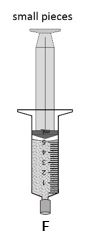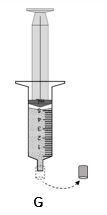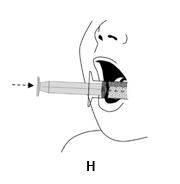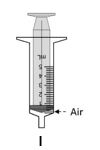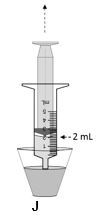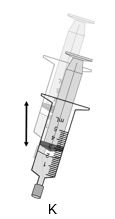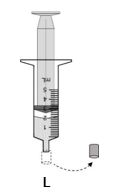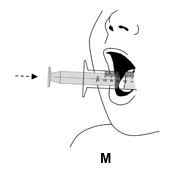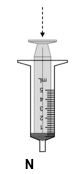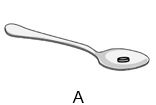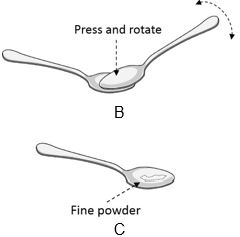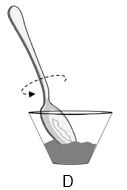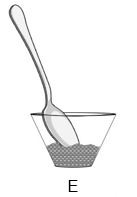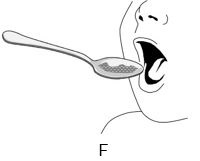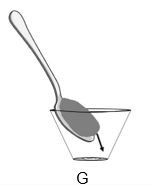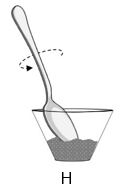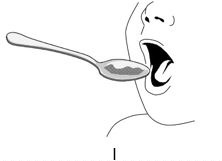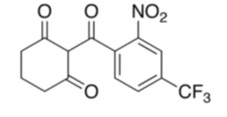 DRUG LABEL: NITYR
NDC: 70709-002 | Form: TABLET
Manufacturer: Cycle Pharmaceuticals Ltd.
Category: prescription | Type: HUMAN PRESCRIPTION DRUG LABEL
Date: 20251222

ACTIVE INGREDIENTS: nitisinone 2 mg/1 1
INACTIVE INGREDIENTS: GLYCERYL DIBEHENATE; LACTOSE MONOHYDRATE

HIGHLIGHTS OF PRESCRIBING INFORMATION

These highlights do not include all the information needed to use NITYR safely and effectively. See full prescribing information for NITYR.
NITYR® (nitisinone) tablets, for oral use
Initial U.S. Approval: 2002

RECENT MAJOR CHANGES

Preparation and Administration Instructions (2.3) 1/2024

1 INDICATIONS AND USAGE

NITYR is a hydroxyphenyl-pyruvate dioxygenase inhibitor indicated for the treatment of adult and pediatric patients with hereditary tyrosinemia type 1 (HT-1) in combination with dietary restriction of tyrosine and phenylalanine. (1)

2 DOSAGE AND ADMINISTRATION

- The recommended starting dosage is 0.5 mg/kg (actual body weight) administered orally twice daily. (2.1)
- Administer NITYR with or without food. (2.1)
- Maintain dietary restriction of tyrosine and phenylalanine when administering NITYR. (2.1)
- The recommended maintenance dosage of NITYR in patients 5 years of age and older who have undetectable serum and urine succinylacetone concentrations after a minimum of 4 weeks on a stable dosage of nitisinone, is 1 to 2 mg/kg once daily. (2.1)
- See the full prescribing information for dosage titration and monitoring. (2.2)
- See the full prescribing information for preparation and administration instructions. (2.2)

3 DOSAGE FORMS AND STRENGTHS

Tablets: 2 mg, 5 mg, 10 mg.

4 CONTRAINDICATIONS

None. (4)

5 WARNINGS AND PRECAUTIONS

Ocular Symptoms, Developmental Delay and Hyperkeratotic Plaques Due To Elevated Plasma Tyrosine Levels: Inadequate restriction of tyrosine and phenylalanine intake can lead to elevations in plasma tyrosine and levels above 500 micromol/L may lead to ocular signs and symptoms, intellectual disability and developmental delay, or painful hyperkeratotic plaques on the soles and palms. (5.1)

- Do not adjust NITYR dosage in order to lower the plasma tyrosine concentration. (5.1)
- Obtain slit-lamp examination prior to treatment and regularly thereafter. Reexamine patients if symptoms develop or tyrosine levels are > 500 micromol/L. Assess plasma tyrosine levels in patients with an abrupt change in neurologic status. (5.1)

Leukopenia and Severe Thrombocytopenia: Monitor platelet and white blood cell counts. (5.2)

6 ADVERSE REACTIONS

Most common adverse reactions (>1%) are elevated tyrosine levels, thrombocytopenia, leukopenia, conjunctivitis, corneal opacity, keratitis, photophobia, eye pain, blepharitis, cataracts, granulocytopenia, epistaxis, pruritus, exfoliative dermatitis, dry skin, maculopapular rash and alopecia. (6.1)

To report SUSPECTED ADVERSE REACTIONS, contact Cycle Pharmaceuticals Ltd. at 1-855-831-5413 or FDA at 1-800-FDA-1088 or www.fda.gov/medwatch.

7 DRUG INTERACTIONS

CYP2C9 Substrates: Increased systemic exposure of these co-administered drugs; reduce the dosage. Additional dosage adjustments may be needed to maintain therapeutic drug concentrations for narrow therapeutic index drugs. (7)
OAT1/OAT3 Substrates: Increased systemic exposure of these co-administered drugs; monitor for potential adverse reactions. (7)

FULL PRESCRIBING INFORMATION

1 INDICATIONS AND USAGE

NITYR® is indicated for the treatment of adult and pediatric patients with hereditary tyrosinemia type 1 (HT-1) in combination with dietary restriction of tyrosine and phenylalanine.

2 DOSAGE AND ADMINISTRATION

2.1 Recommended Dosage

The recommended starting dosage of NITYR is 0.5 mg/kg (actual body weight) administered orally twice daily. Titrate the dose in each individual patient based on biochemical and/or clinical response.

Administer NITYR with or without food [see Clinical Pharmacology (12.3)].

Maintain dietary restriction of tyrosine and phenylalanine when administering NITYR.

Maintenance Dosage

The recommended maintenance dosage of NITYR in patients 5 years of age and older who have undetectable serum and urine succinylacetone concentrations after a minimum of 4 weeks on a stable dosage of nitisinone, is 1 to 2 mg/kg once daily [see Clinical Pharmacology (12.2)].

A maximum total daily dosage of 2 mg/kg may be needed based on the evaluation of all biochemical parameters.

Missed Dose

If a dose of NITYR is missed, do not administer two doses at once to make up for a missed dose. Take the next dose at the scheduled time.

2.2 Dosage Titration and Monitoring

Monitor plasma and/or urine succinylacetone concentrations, liver function parameters and alpha-fetoprotein levels.

Monitor all biochemical parameters more closely (i.e. plasma and/or urine succinylacetone, urine 5-aminolevulinate (ALA), and erythrocyte porphobilinogen (PBG)-synthase activity during initiation of therapy, when switching from twice daily to once daily dosing, or if there is a deterioration in the patient’s condition.

If succinylacetone is still detectable in blood or urine 4 weeks after the start of nitisinone treatment, increase the NITYR dosage to 0.75 mg/kg twice daily. If the biochemical response is satisfactory (undetectable blood and/or urine succinylacetone), the dosage should be adjusted only according to body weight gain and not according to plasma tyrosine levels.

Maintain plasma tyrosine levels below 500 micromol/L by dietary restriction of tyrosine and phenylalanine intake [see Warnings and Precautions (5.1)]. In patients who develop plasma tyrosine levels above 500 micromol/L, assess dietary tyrosine and phenylalanine intake. Do not adjust the NITYR dosage in order to lower the plasma tyrosine concentration.

2.3 Preparation and Administration Instructions

For patients who have difficulty swallowing intact tablets, disintegrate NITYR in water and administer using an oral syringe. For patients who can swallow semi-solid foods, NITYR tablets can be crushed and mixed with applesauce.

Administration of NITYR with other liquids or foods has not been studied and is not recommended.

Preparation and Administration of NITYR with Water in an Oral Syringe:
Do not prepare more than two tablets at once within the same oral syringe.

If patient’s dosage requires more than two tablets, follow the steps below using multiple oral syringes and prescribed number of tablets to achieve the required dose.

One Tablet

1. Remove the plunger from the 5-mL oral syringe and insert a single, intact tablet.

2. Replace the plunger and draw up 2.6 mL of room temperature water.

3. Cap the oral syringe and leave the oral syringe for at least the length of time below:
• 15 minutes for a 2 mg tablet
• 60 minutes for a 5 mg or 10 mg tablet

4. Turn the oral syringe up and down for at least 30 seconds to suspend the material.

5. Inspect the syringe to ensure the tablet has fully disintegrated. If the tablet is not fully disintegrated, leave the oral syringe for an additional 10 minutes. Do not administer unless the tablet has fully disintegrated. Before administration of the suspension, turn the oral syringe up and down for 30 seconds to ensure the particles are suspended.

6. Uncap the oral syringe and administer all the suspension into the patient's mouth. To facilitate full administration, avoid depressing the plunger to the end of the oral syringe and leave a gap between the plunger and the oral syringe.

7. Fill the oral syringe by drawing up 2 mL of water. Shake well and administer while this time fully depressing the plunger. If particles are still present in the syringe, repeat this step.

Two Tablets

1. Remove the plunger from the 5-mL oral syringe and insert two intact tablets.

2. Replace the plunger and draw up 5 mL of room temperature water.

3. Cap the oral syringe and leave it for at least the length of time below:
• 15 minutes for 2 mg tablets
• 60 minutes for 5 mg or 10 mg tablets

4. Turn the oral syringe up and down for at least 30 seconds to suspend the material.

5. Inspect the syringe to ensure the tablets have fully disintegrated. If the tablet is not fully disintegrated, leave the oral syringe for an additional 10 minutes. Do not administer unless the tablet has fully disintegrated. Before administration of the suspension, turn the oral syringe up and down for 30 seconds to ensure the particles are suspended.

6. Uncap the oral syringe and administer all the suspension into the patient's mouth. To facilitate full administration, avoid depressing the plunger to the end of the oral syringe and leave a gap between the plunger and the oral syringe.

7. Fill the oral syringe by drawing up 2 mL of water. Shake well and administer while this time fully depressing the plunger. If particles are still present in the syringe, repeat this step.

Storage Instructions for the NITYR with water in an Oral Syringe

The suspension can be stored at room temperature in the capped oral syringe, protected from direct sunlight for up to 24 hours after adding water to the tablets. Discard after 24 hours.

Preparation and Administration of NITYR Mixed in Applesauce
For patients who can swallow semi-solid food, NITYR can be crushed and mixed with applesauce.

1. Measure approximately one teaspoon of applesauce and transfer it into a clean container (e.g., clean glass).

2. Crush only 1 tablet at a time between two teaspoons forming a fine powder. Repeat this step if more than 1 tablet is needed.

3. Transfer the powder to the applesauce container ensuring all the powder is transferred and no powder residue remains on the teaspoon.

4. Mix the powder into the applesauce until the powder is well dispersed.

5. Administer the entire NITYR-applesauce mixture to the patient immediately or within 2 hours of mixing.

6. To ensure that there is not any remaining NITYR-applesauce mixture, add approximately one teaspoon of applesauce to the same container and administer to the patient.

Storage Instructions for NITYR Mixed in Apple Sauce

The mixture can be stored at room temperature, out of direct sunlight, for up to 2 hours after adding the crushed tablets to the applesauce. Discard after 2 hours.

3 DOSAGE FORMS AND STRENGTHS

Tablets: 2 mg, 5 mg, and 10 mg white to beige, round, flat tablets, which may display light yellow to brown speckles, debossed with “L” on one side and the strength (“2” mg, “5” mg, or “10” mg), on the other side.

4 CONTRAINDICATIONS

None.

5 WARNINGS AND PRECAUTIONS

5.1 Ocular Symptoms, Developmental Delay and Hyperkeratotic Plaques Due To Elevated Plasma Tyrosine Levels

Treatment with NITYR may cause elevated plasma tyrosine levels in patients with HT-1. Inadequate restriction of tyrosine and phenylalanine intake can lead to elevations in plasma tyrosine levels and levels greater than 500 micromol/L may lead to the following:

- Ocular signs and symptoms including corneal ulcers, corneal opacities, keratitis, conjunctivitis, eye pain, and photophobia. All of which have been reported in patients treated with nitisinone [see Adverse Reactions (6.1)]. In a clinical study in a non HT-1 population without dietary restriction and reported tyrosine levels > 500 micromol/L both symptomatic and asymptomatic keratopathies have been observed. Therefore, perform a baseline ophthalmologic examination including slit-lamp examination prior to initiating NITYR treatment and regularly thereafter. Patients who develop photophobia, eye pain, or signs of inflammation such as redness, swelling, or burning of the eyes or tyrosine levels are > 500 micromol/L during treatment with NITYR should undergo slit-lamp reexamination and immediate measurement of the plasma tyrosine concentration.
- Variable degrees of intellectual disability and developmental delay. In patients treated with NITYR who exhibit an abrupt change in neurologic status, perform a clinical laboratory assessment including plasma tyrosine levels.
- Painful hyperkeratotic plaques on the soles and palms.

Maintain concomitant reduction in dietary tyrosine and phenylalanine while on NITYR treatment. In patients with HT-1 who are treated with NITYR and dietary restriction and develop elevated plasma tyrosine levels, assess dietary tyrosine and phenylalanine intake. Do not adjust NITYR dosage in order to lower the plasma tyrosine concentration. Maintain plasma tyrosine levels below 500 micromol/L.

5.2 Leukopenia and Severe Thrombocytopenia

In clinical trials, patients treated with another oral formulation of nitisinone and dietary restriction developed reversible leukopenia (3%), thrombocytopenia (3%), or both (1.5%) [see Adverse Reactions (6.1)]. No patients developed infections or bleeding as a result of the episodes of leukopenia and thrombocytopenia. Monitor platelet and white blood cell counts during NITYR therapy.

6 ADVERSE REACTIONS

Serious and or clinically significant adverse reactions described elsewhere in labeling include:

- Ocular Symptoms, Developmental Delay and Hyperkeratotic Plaques Due To Elevated Plasma Tyrosine Levels [see Warnings and Precautions (5.1)]
- Leukopenia and Severe Thrombocytopenia [see Warnings and Precautions (5.2)]

6.1 Clinical Trials Experience

Because clinical trials are conducted under widely varying conditions, adverse reaction rates observed in the clinical trials of a drug cannot be directly compared to rates in the clinical trials of another drug and may not reflect the rates observed in practice.

The safety of NITYR has been established based on studies of another oral formulation of nitisinone in patients with HT-1 [see Clinical Studies (14)]. Below is a display of the adverse reactions of nitisinone in these studies.

Nitisinone was studied in one open-label, uncontrolled study of 207 patients with HT-1, ages 0 to 22 years at enrollment (median age 9 months), who were diagnosed with HT-1 by the presence of succinylacetone in the urine or plasma. The starting dose of nitisinone was 0.3 to 0.5 mg/kg twice daily, and the dose was increased in some patients to 1 mg/kg twice daily based on weight, biochemical, and enzyme markers. The recommended starting dosage of NITYR is 0.5 mg/kg twice daily [see Dosage and Administration (2.1)]. Median duration of treatment was 22 months (range 0.1 to 80 months).

The most serious adverse reactions reported during nitisinone treatment were thrombocytopenia, leukopenia, porphyria, and ocular/visual complaints associated with elevated tyrosine levels [see Warnings and Precautions (5.1, 5.2)]. Fourteen patients experienced ocular/visual events. The duration of the symptoms varied from 5 days to 2 years. Six patients had thrombocytopenia, three of which had platelet counts 30,000/microL or lower. In 4 patients with thrombocytopenia, platelet counts gradually returned to normal (duration up to 47 days) without change in the nitisinone dose. No patients developed infections or bleeding as a result of the episodes of leukopenia and thrombocytopenia.

Patients with HT-1 are at increased risk of developing porphyric crises, hepatic neoplasms, and liver failure requiring liver transplantation. These complications of HT-1 were observed in patients treated with nitisinone for a median of 22 months during the clinical trial (liver transplantation 13%, liver failure 7%, malignant hepatic neoplasms 5%, benign hepatic neoplasms 3%, porphyria 1%).

The most common adverse reactions reported in the clinical trial are summarized in TABLE 1.

TABLE 1
Most Common Adverse Reactions* in Patients with HT-1 Treated with Nitisinone**
Elevated tyrosine levels | >10%
Leukopenia | 3%
Thrombocytopenia | 3%
Conjunctivitis | 2%
Corneal Opacity | 2%
Keratitis | 2%
Photophobia | 2%
Eye Pain | 1%
Blepharitis | 1%
Cataracts | 1%
Granulocytopenia | 1%
Epistaxis | 1%
Pruritus | 1%
Exfoliative Dermatitis | 1%
Dry Skin | 1%
Maculopapular Rash | 1%
Alopecia | 1%
*reported in at least 1% of patients; ** another oral formulation of nitisinone

Adverse reactions reported in less than 1% of the patients, included death, seizure, brain tumor, encephalopathy, hyperkinesia, cyanosis, abdominal pain, diarrhea, enanthema, gastrointestinal hemorrhage, melena, elevated hepatic enzymes, liver enlargement, hypoglycemia, septicemia, and bronchitis.

7 DRUG INTERACTIONS

Nitisinone is a moderate CYP2C9 inhibitor, a weak CYP2E1 inducer and an inhibitor of OAT1/OAT3. TABLE 2 includes drugs with clinically significant drug interactions when administered concomitantly with NITYR and instructions for preventing or managing them.

TABLE 2. Clinically Significant Interactions Affecting Co-Administered Drugs

Sensitive CYP2C9 Substrates (e.g., celecoxib, tolbutamide) or CYP2C9 Substrates with a Narrow Therapeutic Index (e.g., phenytoin, warfarin)
Clinical Impact | Increased exposure of the co-administered drugs metabolized by CYP2C9. [see Clinical Pharmacology (12.3)]
Prevention or Management | Reduce the dosage of the co-administered drugs metabolized by CYP2C9 drug by half. Additional dosage adjustments may be needed to maintain therapeutic drug concentrations for narrow therapeutic index drugs. See prescribing information for those drugs.
OAT1/OAT3 Substrates (e.g., adefovir, ganciclovir, methotrexate)
Clinical Impact | Increased exposure of the interacting drug. [see Clinical Pharmacology (12.3)]
Prevention or Management | Monitor for potential adverse reactions related to the co-administered drug.

8 USE IN SPECIFIC POPULATIONS

8.1 Pregnancy

Risk Summary
Limited available data with nitisinone use in pregnant women are not sufficient to determine a drug-associated risk of adverse developmental outcomes. Animal reproduction studies have been conducted for nitisinone. In these studies, nitisinone was administered to mice and rabbits during organogenesis with oral doses of nitisinone up to 20 and 8-times respectively, the recommended initial dose of 1 mg/kg/day. In mice, nitisinone caused incomplete skeletal ossification of fetal bones and decreased pup survival at doses 0.4 times the recommended initial dose, and increased gestational length at doses 4 times the recommended initial dose. In rabbits, nitisinone caused maternal toxicity and incomplete skeletal ossification of fetal bones at doses 1.6 times the recommended initial dose (see Data).

The background risk of major birth defects and miscarriage for the indicated population are unknown. In the U.S. general population, the estimated background risk of major birth defects and miscarriage in clinically recognized pregnancies is 2 to 4% and 15 to 20%, respectively.

Data
Animal Data

Reproduction studies have been performed in mice at oral doses of about 0.4, 4 and 20 times the recommended initial dose (1 mg/kg/day) and in rabbits at oral doses of about 1.6, 4 and 8 times the recommended initial dose based on the body surface area. In mice, nitisinone has been shown to cause incomplete skeletal ossification of fetal bones at 0.4, 4 and 20 times the recommended initial dose, increased gestational length at 4 and 20 times the recommended initial dose, and decreased pup survival at 0.4 times the recommended initial dose based on the body surface area. In rabbits, nitisinone caused incomplete skeletal ossification of fetal bones at 1.6, 4 and 8 times the recommended initial dose based on the body surface area.

8.2 Lactation

Risk Summary
There are no data on the presence of nitisinone in human milk, the effects on the breastfed infant, or the effects on milk production. Data suggest that nitisinone is present in rat milk due to findings of ocular toxicity and lower body weight seen in drug naive nursing rat pups. The development and health benefits of breastfeeding should be considered along with the mother’s clinical need for NITYR and any potential adverse effects on the breastfed infant from NITYR or from the underlying maternal condition.

8.4 Pediatric Use

The safety and effectiveness of nitisinone have been established for the treatment of HT-1 in combination with dietary restriction of tyrosine and phenylalanine in pediatric patients. Use of NITYR for this indication is supported by evidence from one open-label, uncontrolled clinical study conducted with another oral formulation of nitisinone in 207 patients with HT-1 ages 0 to 22 years (median age 9 months) [see Clinical Studies (14)].

8.5 Geriatric Use

Clinical studies of nitisinone did not include any subjects aged 65 and over to determine whether they respond differently from younger subjects. No pharmacokinetic studies of nitisinone have been performed in geriatric patients. In general, dose selection for an elderly patient should be cautious reflecting the greater frequency of decreased hepatic, renal, or cardiac function, and of concomitant disease or other drug therapy in this patient population.

11 DESCRIPTION

NITYR (nitisinone) is a hydroxyphenyl-pyruvate dioxygenase inhibitor.

Nitisinone occurs as a white to yellowish-white, crystalline powder. It is practically insoluble in water, soluble in 2M sodium hydroxide and in methanol, and sparingly soluble in alcohol.

The chemical name of nitisinone is 2-(2-nitro-4-trifluoromethylbenzoyl) cyclohexane-1,3-dione. The empirical formula is C14H10F3NO5 and the molecular weight is 329.23. The structural formula is:

Each NITYR (nitisinone) tablet contains 2, 5 or 10 mg of nitisinone. Inactive ingredients are: glyceryl dibehenate, and lactose monohydrate. NITYR tablets are intended for oral administration.

12 CLINICAL PHARMACOLOGY

12.1 Mechanism of Action

Nitisinone is a competitive inhibitor of 4-hydroxyphenyl-pyruvate dioxygenase, an enzyme upstream of fumarylacetoacetate hydrolase (FAH) in the tyrosine catabolic pathway. By inhibiting the normal catabolism of tyrosine in patients with HT-1, nitisinone prevents the accumulation of the catabolic intermediates maleylacetoacetate and fumarylacetoacetate. In patients with HT-1, these catabolic intermediates are converted to the toxic metabolites succinylacetone and succinylacetoacetate, which are responsible for the observed liver and kidney toxicity. Succinylacetone can also inhibit the porphyrin synthesis pathway leading to the accumulation of 5-aminolevulinate, a neurotoxin responsible for the porphyric crises characteristic of HT-1.

12.2 Pharmacodynamics

In a clinical study, patients with HT-1 were diagnosed by the presence of succinylacetone in urine or plasma and treated with another oral formulation of nitisinone [see Clinical Studies (14)]. In all 186 patients whose urine succinylacetone was measured, the urinary succinylacetone concentration decreased to less than 1 mmol/mol creatinine, the lower limit of quantitation. The median time to normalization of urine succinylacetone was 0.3 months. The probability of recurrence of abnormal values of urine succinylacetone was 1% at a nitisinone concentration of 37 micromol/L (95% confidence interval: 23, 51 micromol/L). In 87% (150/172) of patients whose plasma succinylacetone was measured, the plasma succinylacetone concentration decreased to less than 0.1 micromol/L, the lower limit of quantitation. The median time to normalization of plasma succinylacetone was 3.9 months.

In another study, comparing two dosing regimens of another oral formulation of nitisinone, succinylacetone was measured in urine and/or blood in 16 patients with HT-1 aged 5 years to 24 years. All study patients were on a stable nitisinone daily dosage (0.4 mg/kg/day to 1 mg/kg/day) during both study dosing regimens. After at least 4 weeks of twice daily dosing with nitisinone, both the urine and/or blood succinylacetone concentrations were below the limit of quantitation for the assay. Patients were then switched to once daily dosing with the same total daily dosage of nitisinone and blood and/or urine succinylacetone concentrations remained undetectable when measured following at least 4 weeks of treatment with once daily dosing.

Nitisinone inhibits catabolism of the amino acid tyrosine and can result in elevated plasma levels of tyrosine. Therefore, treatment with nitisinone requires restriction of the dietary intake of tyrosine and phenylalanine to prevent the toxicity associated with elevated plasma levels of tyrosine [see Warnings and Precautions (5.1)].

12.3 Pharmacokinetics

The single-dose pharmacokinetics of nitisinone have been studied for NITYR tablets in healthy adult subjects.

Absorption
The pharmacokinetic characteristics following single oral administration of 10 mg NITYR under fasting conditions are shown in TABLE 3.

TABLE 3. Geometric Mean Pharmacokinetic Parameters in Healthy Subjects Following a Single Oral 10 mg Dose of NITYR Under Fasting Conditions

Treatment | Cmax (ng/mL) [range] | Tmax* (h) [range] | AUC 0-120h (ng•h/mL) [range]
Single 10 mg NITYR Tablet fasted (n=23) | 1278 [780 to 1649] | 3.5; [1.0 to 4.0] | 77874 [42335 to 104211]
* presented as median [range]

Effect of Food: In a food effect study, a high-fat and high-calorie breakfast (973.6 cal distributed in carbohydrate 250.1 cal, proteins 157 cal, fat 566.5 cal) did not significantly affect the total exposure (AUC0-120h) and Cmax of nitisinone following single oral administration of 10 mg NITYR. The median Tmax was delayed to 6 hours under fed conditions [see Dosage and Administration (2.2)].

Distribution
In vitro binding of nitisinone to human plasma proteins is greater than 95% at 50 micromolar concentration. For NITYR, the arithmetic mean (SD) apparent volume of distribution of nitisinone is 8.2 (1.6) L in healthy subjects (n=23).

Elimination
For NITYR, the arithmetic mean (SD) terminal half-life of nitisinone is 59.3 (8.9) hours in healthy subjects (n=23).

Metabolism: In vitro studies have shown that nitisinone is relatively stable in human liver microsomes with minor metabolism possibly mediated by CYP3A4 enzyme.

Excretion: Renal elimination of nitisinone is of minor importance, since the mean of the fraction of dose excreted as unchanged nitisinone in the urine (fe(%)) was 3.0% (n=3) following multiple oral doses of 80 mg daily in healthy subjects. The estimated mean (CV%) renal clearance of nitisinone was 0.003 L/h (25%).

Drug Interaction Studies
Nitisinone does not inhibit CYP2D6. Nitisinone is a moderate inhibitor of CYP2C9, and a weak inducer of CYP2E1 (TABLE 4). Nitisinone is an inhibitor of OAT1/3 (TABLE 4).

TABLE 4. Percent Change in AUC0-∞ and Cmax for Co-administered Drugs in the Presence of Nitisinone in 18 Healthy Subjects

Co-administered Drug a | Dose of Co-administered Drug (Route of Administration) | Effect of Nitisinone on the Pharmacokinetics of Co-administered Drug b
Co-administered Drug a | Dose of Co-administered Drug (Route of Administration) | AUC0-∞ | Cmax
CYP2C9 Substrate Tolbutamide c | 500 mg (oral) | 131%↑ | 16%↑
CYP2E1 Substrate; Chlorzoxazone | 250 mg (oral) | 27%↓ | 18%↓
OAT1/3 Substrate Furosemide | 20 mg (intravenous) | 72%↑ | 12%↑

↑= Increased; ↓= Decreased

a The interacting drug was administered alone on Day 1 and together with nitisinone on Day 17.
b Multiple doses of 80 mg nitisinone were administered daily alone from Day 3 to Day 16.
c 16 subjects in Period 2 received nitisinone and tolbutamide while 18 subjects in Period 1 received nitisinone alone.

In Vitro Studies Where Drug Interaction Potential Was Not Further Evaluated Clinically

In vitro studies showed that nitisinone does not inhibit CYP1A2, 2C19, or 3A4. Nitisinone does not induce CYP1A2, 2B6 or 3A4/5. Nitisinone does not inhibit P-gp, BCRP, OATP1B1, OATP1B3 and OCT2-mediated transports at therapeutically relevant concentrations.

13 NONCLINICAL TOXICOLOGY

13.1 Carcinogenesis, Mutagenesis, Impairment of Fertility

The carcinogenic potential of nitisinone was assessed in a 26-week oral (gavage) carcinogenicity study in Tg.rasH2 mice. There were no drug-related neoplastic findings in male or female Tg.rasH2 mice at doses up to 100 mg/kg/ day nitisinone (approximately 8.1 times the recommended initial dose of 1 mg/kg/day on a body surface area basis).

Nitisinone was not genotoxic in the Ames test and the in vivo mouse liver unscheduled DNA synthesis (UDS) test. Nitisinone was mutagenic in the mouse lymphoma cell (L5178Y/TK+/-) forward mutation test and in an in vivo mouse bone marrow micronucleus test.

In a single dose-group study in rats given 100 mg/kg (16.2 times the recommended initial dose of 1 mg/kg/day on a body surface area basis), reduced litter size, decreased pup weight at birth, and decreased survival of pups after birth was demonstrated.

14 CLINICAL STUDIES

The safety and efficacy of NITYR have been established based on studies of another oral formulation of nitisinone in patients with HT-1. Below is a display of the results of these studies.

The efficacy and safety of nitisinone in patients with HT-1 was evaluated in one open-label, uncontrolled study of 207 patients with HT-1, ages 0 to 22 years at enrollment (median age 9 months). Patients were diagnosed with HT-1 by the presence of succinylacetone in the urine or plasma. All patients were treated with nitisinone at a starting dose of 0.3 to 0.5 mg/kg orally twice daily, and the dose was increased in some patients to 1 mg/kg twice daily based on weight, liver and kidney function tests, platelet count, serum amino acids, urinary phenolic acid, plasma and urine succinylacetone, erythrocyte PBG- synthase, and urine 5-ALA. The median duration of treatment was 22 months (range less than 1 month to 80 months). Efficacy was assessed by comparison of survival and incidence of liver transplant to historical controls.

For patients presenting with HT-1 younger than 2 months of age who were treated with dietary restriction and nitisinone, 2- and 4-year survival probabilities were 88% and 88%, respectively. Data from historical controls showed that patients presenting with HT-1 younger than 2 months of age treated with dietary restriction alone had 2- and 4-year survival probabilities of 29% and 29%, respectively. For patients presenting between 2 months and 6 months of age who were treated with dietary restrictions and nitisinone, 2-and 4-year survival probabilities were 94% and 94%, respectively. Data for historical controls showed that patients presenting with HT-1 between 2 months and 6 months of age treated with dietary restriction alone had 2-and 4-year survival probabilities of 74% and 60%, respectively.

The effects of nitisinone on urine and plasma succinylacetone, porphyrin metabolism, and urinary alpha-1-microglobulin were also assessed in this clinical study.

Porphyria-like crisis were reported in 3 patients (0.3% of cases per year) during the clinical study. This compares to an incidence of 5 to 20% of cases per year expected as part of the natural history of the disorder. An assessment of porphyria-like crises was performed because these events are commonly reported in patients with HT-1 who are not treated with nitisinone.

Urinary alpha-1-microglobulin, a proposed marker of proximal tubular dysfunction, was measured in 100 patients at baseline. The overall median pretreatment level was 4.3 grams/mol creatinine. After one year of treatment in a subgroup of patients (N=100), overall median alpha-1-microglobulin decreased by 1.5 grams/mol creatinine. In patients 24 months of age and younger in whom multiple values were available (N=65), median alpha-1-microglobulin levels decreased from 5 to 3 grams/mol creatinine (reference value for age less than or equal to 12 grams/mol creatinine). In patients older than 24 months in whom multiple values were available (N=35), median alpha-1-microglobulin levels decreased from 2.8 to 2 grams/mol creatinine (reference for age less than or equal to 6 grams/mol creatinine).

16 HOW SUPPLIED/STORAGE AND HANDLING

How Supplied

NITYR (nitisinone) tablet is white to beige, round, flat which may display light yellow to brown speckles, debossed with the “strength” in mg on one side and “L” on the other side. Each tablet contains 2, 5 or 10 mg nitisinone.

NITYR is supplied in a high-density polyethylene (HDPE) square bottle with a child-resistant tamper-evident polypropylene (PP) screw cap. Each bottle contains 60 tablets.

2 mg tablets: NDC 70709-002-60

5 mg tablets: NDC 70709-005-60

10 mg tablets: NDC 70709-000-60

Storage and Handling

Store NITYR tablets at room temperature between 20°C to 25°C (68°F to 77°F); excursions permitted between 15°C and 30°C (59°F and 86°F) [see USP Controlled Room Temperature].

Pharmacist: Dispense in tight and light resistant container as defined in USP.
Dispense 5-mL oral syringe with a cap to use for preparation.

17 PATIENT COUNSELING INFORMATION

Advise the patient to read the FDA-approved patient labeling (Instructions for Use).

Dosage and Administration Instructions

Advise the patient or caregiver to:

- Combine NITYR with dietary restriction of tyrosine and phenylalanine.
- Take NITYR with or without food.
- Disintegrate the tablet(s) in water if patient has difficulty swallowing intact tablet(s), or if patient can swallow semi-solid foods, crush the tablet(s) and mix with applesauce.

[see Dosage and Administration (2)]

How Supplied/Storage and Handling

Advise the patient or caregiver to store NITYR in the container that it is dispensed in and keep the container tightly closed [see How Supplied/Storage and Handling (16)].

Ocular Symptoms, Developmental Delay and Hyperkeratotic Plaques Due to Elevated Plasma Tyrosine Levels

Advise the patient or caregiver that inadequate dietary restriction may be associated with ocular signs and symptoms, intellectual disability and developmental delay, and painful hyperkeratotic plaques on the soles and palms. Additionally, advise the patient or caregiver of the need to maintain dietary restriction of tyrosine and phenylalanine and to report any unexplained ocular, neurologic, or other symptoms promptly to their healthcare provider [see Warnings and Precautions (5.1)].

Manufactured by:
PCI Pharma Services
23-24 Tafarnaubach Industrial Estate
Tredegar, Gwent
NP22 3AA, United Kingdom

Rivopharm SA
Centro Insema
6928 Manno, Switzerland

Marketed by:
Cycle Pharmaceuticals Ltd
The Broers Building
21 JJ Thomson Ave
Cambridge, CB3 0FA, United Kingdom

Patented: see www.cyclepharma.com/product-patent-information

PATIENT INFORMATION

INSTRUCTIONS FOR USE
NITYR® (ni-TIR)
(nitisinone)
tablets, for oral use

This Instructions for Use contains information on how to take NITYR tablets using an oral syringe or mixed in applesauce.

Read this Instructions for Use before you start giving or taking NITYR and each time you get a refill, since there may be new information. This information does not take the place of talking to your healthcare provider about your medical condition or your treatment.

- People who have a problem swallowing NITYR tablets whole, including children, can take NITYR tablets mixed with water in an oral (by mouth) syringe or crushed and mixed with applesauce. NITYR tablets should not be mixed in any other liquid or food.
- Follow the diet restrictions for tyrosine and phenylalanine that your healthcare provider has given you during treatment with NITYR.
- NITYR can be taken with or without food.

Important Information You Need to Know Before Taking NITYR Using an Oral Syringe

- Prepare only 1 or 2 NITYR tablets in an oral syringe at one time.
- Each tablet is white to beige in color and can have yellow to brown tiny specks.
- Use a 5 mL oral syringe with a cap (see below) to prepare NITYR tablets in an oral syringe. Ask your pharmacist for your oral syringe. You may need more than one 5 mL oral syringe if you take more than 2 NITYR tablets for your prescribed dose.
- Use only room temperature water to prepare NITYR tablets in an oral syringe.
- Wash your hands well before preparing NITYR tablets using an oral syringe.
- Talk to your healthcare provider or pharmacist if you have questions about NITYR tablets or how to use the oral syringe. You can also contact CYCLE VITA by calling the United States (U.S.) toll free phone number 1-888-360-8482.

Before preparing NITYR using an oral syringe

Lay out the prescribed number of NITYR tablets and syringes for your dose. Place the tablet or tablets on a clean flat surface.

How to prepare and take 1 NITYR tablet using a 5 mL oral syringe:

Step 1. Remove the cap from the 5 mL oral syringe.
Step 2. Remove the plunger from the oral syringe and place 1 whole NITYR tablet inside the oral syringe (See Figure A).

Step 3. Replace the plunger (See Figure B).

Step 4. Draw up 2.6 mL of room temperature water into the oral syringe. Each line on the barrel of the syringe is 0.2 mL. There may be some air in the oral syringe. Leave the air in the oral syringe (See Figure C).

Step 5. Replace the cap on the oral syringe and note the time. Let the oral syringe sit for at least the length of time below:
• 15 minutes for a 2 mg tablet
• 60 minutes for a 5 mg or 10 mg tablet
(See Figure D)

Step 6. Turn the oral syringe up and down for at least 30 seconds (See Figure E).

Step 7. Check the oral syringe to see if the NITYR tablet has broken apart into very small pieces and the pieces are evenly spread through the water (suspension) (See Figure F). Do not take the suspension if there are any large pieces of the NITYR tablet in the suspension or if there are any pieces of the tablet that are not evenly spread through the water.
If there are any pieces of the tablet that are not evenly spread through the water, let the oral syringe sit for 10 minutes.
Before giving the suspension, turn the oral syringe up and down for 30 seconds to continue to spread the pieces of NITYR tablet in the suspension.

Step 8. Remove the cap from the oral syringe (See Figure G).

Step 9. Place the tip of the oral syringe in the mouth. If giving to a child, place the tip of the oral syringe along the inner cheek of the child’s mouth (See Figure H).

Step 10. While keeping the oral syringe in the mouth, slowly push down on the plunger until a small amount of air is left in the oral syringe, between the plunger and the tip of the oral syringe (See Figure I). Do not press the plunger all the way down to the end of the syringe.

Step 11. Draw up an additional 2 mL of water into the oral syringe (See Figure J).

Step 12. Replace the cap on the oral syringe. Shake well to spread the remaining tablet pieces evenly through the water in the oral syringe (See Figure K).

Step 13. Remove the cap from the oral syringe (See Figure L).

Step 14. Place the tip of the oral syringe in the mouth. If giving to a child, place the tip of the oral syringe along the inner cheek of the child’s mouth (See Figure M).

Step 15. While keeping the oral syringe in the mouth, slowly push down on the plunger until the oral syringe is empty (See Figure N). In case any pieces of the tablet are still present in the oral syringe, repeat steps 11 through 15.

Step 16. After use, remove the plunger from the syringe barrel. Rinse the syringe and the plunger with water after each use and let it dry. Do not replace the plunger into the barrel of the oral syringe until ready to use again to allow it to dry. Do not throw away the oral syringe or plunger.

If you are not taking the water and NITYR tablet suspension as soon as it is prepared, complete steps 1 through 5. When you are ready to take the suspension, complete steps 6 through 16.

How to prepare and take 2 NITYR tablets using a 5 mL oral syringe:

Step 1. Remove the cap from the 5 mL oral syringe.
Step 2. Remove the plunger from the oral syringe and place 2 whole NITYR tablets inside the oral syringe (See Figure A).

Step 3. Replace the plunger (See Figure B).

Step 4. Draw up 5 mL of room temperature water into the oral syringe. Each line on the barrel of the syringe is 0.2 mL. There may be some air in the oral syringe. Leave the air in the oral syringe (See Figure C).

Step 5. Replace the cap on the oral syringe and note the time. Let the oral syringe sit for at least the length of time below:
• 15 minutes for 2 mg tablets
• 60 minutes for 5 mg or 10 mg tablets
(See Figure D).

Step 6. Turn the oral syringe up and down for at least 30 seconds (See Figure E).

Step 7. Check the oral syringe to see if the NITYR tablets have broken apart into very small pieces and the pieces are evenly spread through the water (suspension) (See Figure F). Do not take the suspension if there are any large pieces of the NITYR tablets in the suspension or if there are any pieces of the tablets that are not evenly spread through the water.
If there are any pieces of the tablets that are not evenly spread through the water, let the oral syringe sit for 10 minutes.
Before giving the suspension, turn the oral syringe up and down for 30 seconds to continue to spread the pieces of NITYR tablets in the suspension.

Step 8. Remove the cap from the oral syringe (See Figure G).

Step 9. Place the tip of the oral syringe in the mouth. If giving to a child, place the tip of the oral syringe along the inner cheek of the child’s mouth (See Figure H).

Step 10. While keeping the oral syringe in the mouth, slowly push down on the plunger until a small amount of air is left in the oral syringe, between the plunger and the tip of the oral syringe (See Figure I). Do not press all the way down on the plunger.

Step 11. Draw up 2 mL of water into the oral syringe (See Figure J).

Step 12. Replace the cap on the oral syringe. Shake well to spread the remaining tablet pieces evenly through the water in the oral syringe (See Figure K).

Step 13. Remove the cap from the oral syringe (See Figure L).

Step 14. Place the tip of the oral syringe in the mouth. If giving to a child, place the tip of the oral syringe along the inner cheek of the child’s mouth (See Figure M).

Step 15. While keeping the oral syringe in the mouth, slowly push down on the plunger until the oral syringe is empty (See Figure N). In case any pieces of the tablets are still present in the oral syringe, repeat steps 11 through 15.

Step 16. After use, remove the plunger from the oral syringe barrel. Rinse the oral syringe with water after each use and let it dry. Do not replace the plunger into the barrel of the oral syringe until ready to use again to allow it to dry. Do not throw away the oral syringe.

If you are not taking the water and NITYR tablets suspension as soon as it is prepared, complete steps 1 through 5. When you are ready to take the suspension, complete steps 6 through 16.

How to prepare and take more than 2 NITYR tablets using an oral syringe:

If more than two NITYR tablets are needed for the prescribed dose follow the instructions for “How to prepare and take 1 NITYR tablet using an oral syringe” and “How to prepare and take 2 NITYR tablets using an oral syringe” until you get your prescribed dose. You should not add more than 2 tablets to one syringe at a time.

How to prepare and take NITYR tablets in applesauce:

- Wash your hands well before preparing NITYR tablets in applesauce.
- Crush only 1 NITYR tablet at a time.

Step 1. Measure about 1 teaspoon of applesauce and put it into a clean container, such as a glass or bowl.
Step 2. Place 1 NITYR tablet onto a metal teaspoon (See Figure A).

Step 3. Crush 1 tablet at a time between two spoons (See Figure B) until the tablet is crushed to a fine powder (See Figure C).

Step 4. Carefully place all of the NITYR tablet powder from the teaspoon into the clean container of applesauce. Be sure that no tablet powder remains on the teaspoon (See Figure D).

Step 5. If the prescribed dose is more than 1 tablet, repeat Steps 2 and 3, placing all of the NITYR tablet powder together in the container with the applesauce. You do not need to add more applesauce at this time if you take more than 1 tablet.
Step 6. Stir the NITYR tablet powder and the applesauce until all of the tablet powder is mixed well in the applesauce (See Figure E).

Step 7. Remove the NITYR tablet powder and applesauce mixture from the container using a teaspoon and swallow the mixture right away or within 2 hours of mixing (See Figure F). Repeat this step until no mixture is left in the container.

Step 8. Measure another 1 teaspoon of applesauce and place it in the container used to mix the NITYR tablet powder and applesauce (See Figure G).

Step 9. Stir the fresh applesauce with the remaining NITYR tablet powder and applesauce mixture until they are mixed well (See Figure H).

Step 10. Remove the NITYR tablet and applesauce mixture from the container using a teaspoon and swallow the mixture right away (See Figure I). Repeat this step until no mixture or powder is left in the container.

Storing NITYR

- NITYR tablets do not need to be refrigerated.
- Store NITYR tablets at room temperature between 68°F to 77°F (20°C to 25°C).
- Store NITYR tablets in the container that it comes in and keep the container tightly closed.
- Keep NITYR tablets and NITYR that has been prepared in an oral syringe with water or in applesauce out of direct sunlight.

After adding water to the tablet in the oral syringe you can keep NITYR tablet suspension at room temperature for 24 hours. Store the suspension in the oral syringe with the cap on and out of direct sunlight until use. The suspension does not need to be refrigerated. Throw away any suspension that is not used within 24 hours after adding water to the tablets in the oral syringe. Empty the syringe in the drain and throw away (dispose of) the syringe by placing it in a trash can.

Take the NITYR tablet and applesauce mixture within 2 hours after adding the NITYR tablet powder to the applesauce. Store the NITYR tablet and applesauce mixture at room temperature and out of direct sunlight until use. The mixture does not need to be refrigerated. Throw away any mixture that is not used within 2 hours after mixing in a trash can.

Keep NITYR and all medicines out of the reach of children.

What are the ingredients in NITYR?

Active ingredient: nitisinone

Inactive ingredients: glyceryl dibehenate and lactose monohydrate

Talk to your healthcare provider or pharmacist if you have questions about NITYR tablets or how to use the oral syringe. You can also contact the CYCLE VITA on the U.S. toll free number 1-888-360-8482.
For more information visit: www.nityr.us

Manufactured by:

PCI Pharma Services
23-24 Tafarnaubach Industrial Estate
Tredegar, Gwent
NP22 3AA, United Kingdom

Rivopharm SA
Centro Insema
6928 Manno, Switzerland

Marketed by:
Cycle Pharmaceuticals Ltd
The Broers Building
21 JJ Thomson Ave
Cambridge, CB3 0FA, United Kingdom

This Instructions for Use has been approved by the U.S. Food and Drug Administration.

Revised: 1/2024

Principal Display Panel - 2 mg Carton Label

NDC 70709-002-60

NITYR®
(nitisinone) tablets

2 mg

For Oral Use

Store at room temperature between 20°C to 25°C (68°F to 77°F), excursions permitted to 15°C and 30°C (59° and 86°F). (See USP Controlled Room Temperature).

Rx only 60 tablets

Principal Display Panel – 2 mg Bottle Label

NDC 70709-002-60

NITYR®
(nitisinone) tablets

2 mg

For Oral Use

Store at room temperature between 20°C to 25°C (68°F to 77°F).

Rx only 60 tablets

Principal Display Panel - 5 mg Carton Label

NDC 70709-005-60

NITYR®
(nitisinone) tablets

5 mg

For Oral Use

Store at room temperature between 20°C to 25°C (68°F to 77°F), excursions permitted to 15°C and 30°C (59° and 86°F). (See USP Controlled Room Temperature).

Rx only 60 tablets

Principal Display Panel – 5 mg Bottle Label

NDC 70709-005-60

NITYR®
(nitisinone) tablets

5 mg

For Oral Use

Store at room temperature between 20°C to 25°C (68°F to 77°F).

Rx only 60 tablets

Principal Display Panel - 10 mg Carton Label

NDC 70709-000-60

NITYR®
(nitisinone) tablets

10 mg

For Oral Use

Store at room temperature between 20°C to 25°C (68°F to 77°F), excursions permitted to 15°C and 30°C (59° and 86°F). (See USP Controlled Room Temperature).

Rx only 60 tablets

Principal Display Panel – 10 mg Bottle Label

NDC 70709-000-60

NITYR®
(nitisinone) tablets

10 mg

For Oral Use

Store at room temperature between 20°C to 25°C (68°F to 77°F).

Rx only 60 tablets